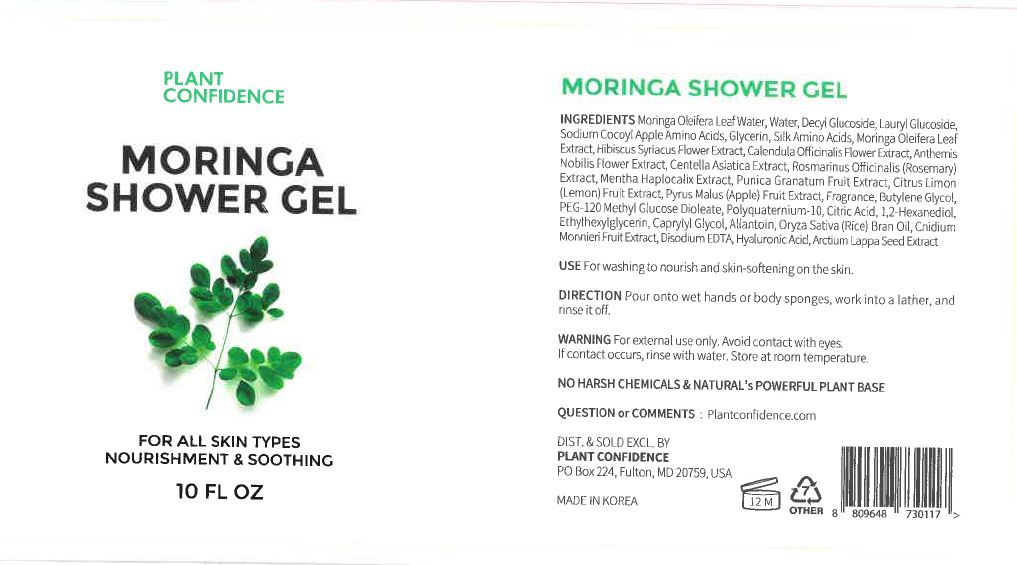 DRUG LABEL: Moringa ShowerGel
NDC: 71484-0009 | Form: GEL
Manufacturer: Ddoruroo Co., Ltd.
Category: otc | Type: HUMAN OTC DRUG LABEL
Date: 20200305

ACTIVE INGREDIENTS: MORINGA OLEIFERA LEAF 1 g/100 mL; AMINO ACIDS, SILK 1.2 g/100 mL
INACTIVE INGREDIENTS: WATER

Drug Facts

ACTIVE INGREDIENT

Silk Amino Acids
Moringa Oleifera Leaf Extract
Hibiscus Syriacus Flower Extract
Calendula Officinalis Flower Extract
Anthemis Nobilis Flower Extract
Centella Asiatica Extract
Rosmarinus Officinalis (Rosemary) Extract
Mentha Haplocalix Extract
Punica Granatum Fruit Extract
Citrus Limon (Lemon) Fruit Extract
Pyrus Malus (Apple) Fruit Extract

Allantoin
Oryza Sativa (Rice) Bran Oil
Cnidium Monnieri Fruit Extract
Hyaluronic Acid
Arctium Lappa Seed Extract

INACTIVE INGREDIENT

Moringa Oleifera Leaf Water
Water
Decyl Glucoside
Lauryl Glucoside
Sodium Cocoyl Apple Amino Acids
Glycerin

Fragrance
Butylene Glycol
PEG-120 Methyl Glucose Dioleate
Polyquaternium-10
Citric Acid
1,2-Hexanediol
Ethylhexylglycerin
Caprylyl glycol

hyaluronic acid

PURPOSE

for washing to nourish and skin softening on the skin

KEEP OUT OF REACH OF THE CHILDREN

INDICATIONS AND USAGE

pour onto wet hands or body sponges, work into a lather, and rinse it off

WARNINGS

1. Do not use in the following cases (Eczema and scalp wounds)
2.Side Effects
1)Due to the use of this druf if rash, irritation, itching and symptopms of hypersnesitivity occur dicontinue use and consult your phamacisr or doctor
3.General Precautions
1)If in contact with the eyes, wash out thoroughty with water If the symptoms are servere, seek medical advice immediately
2)This product is for exeternal use only. Do not use for internal use
4.Storage and handling precautions
1)If possible, avoid direct sunlight and store in cool and area of low humidity
2)In order to maintain the quality of the product and avoid misuse
3)Avoid placing the product near fire and store out in reach of children

DOSAGE AND ADMINISTRATION

for external use only